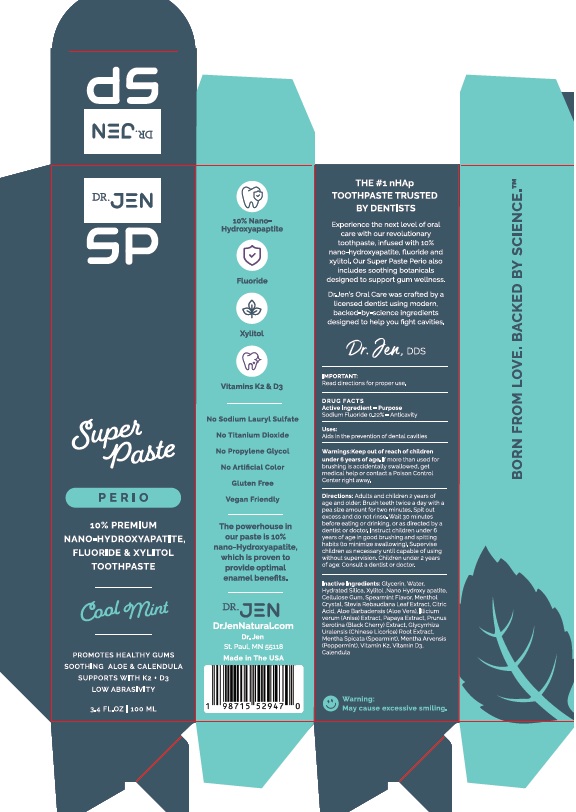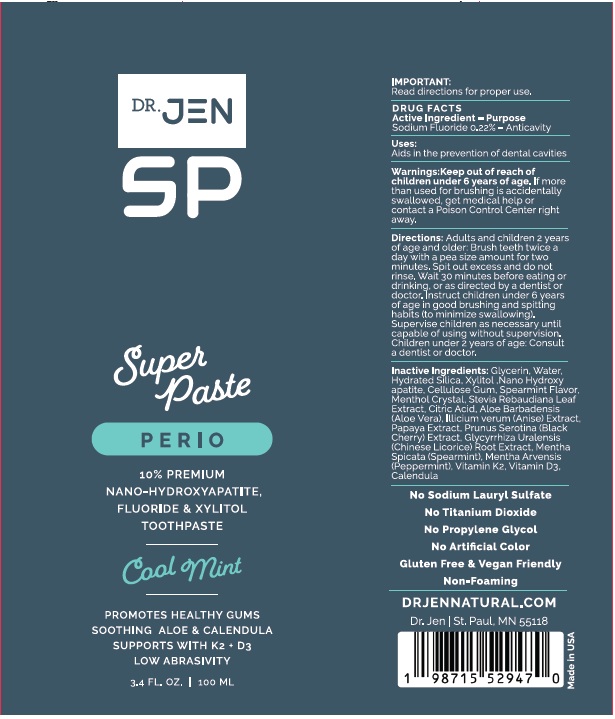 DRUG LABEL: Dr. Jen SuperPaste Perio
NDC: 84181-358 | Form: PASTE, DENTIFRICE
Manufacturer: Dr Jen Natural, LLC
Category: otc | Type: HUMAN OTC DRUG LABEL
Date: 20251204

ACTIVE INGREDIENTS: SODIUM FLUORIDE 0.22 g/100 mL
INACTIVE INGREDIENTS: GLYCERIN; WATER; HYDRATED SILICA; XYLITOL; TRIBASIC CALCIUM PHOSPHATE; CELLULOSE GUM; MENTHOL, UNSPECIFIED FORM; STEVIA REBAUDIANA LEAF; CITRIC ACID; ALOE VERA LEAF; ILLICIUM VERUM WHOLE; PAPAYA; BLACK CHERRY; GLYCYRRHIZA URALENSIS ROOT; SPEARMINT; PEPPERMINT; MENAQUINONE 6; CHOLECALCIFEROL; CALENDULA OFFICINALIS FLOWER

Dr. Jen SuperPaste Perio

OTHER SAFETY INFORMATION

IMPORTANT:

Read directions for proper use.

DRUG FACTS

Active Ingredient
Sodium Fluoride 0.22%

Purpose:
Sodium Fluoride - Anticavity

INDICATIONS AND USAGE

Use: Aids in the prevention of dental cavities

Warnings:

Keep out of reach of children under 6 years of age.
If more than used for brushing is
accidentally swallowed, get medical help or
contact a Poison Control Center right away.

DOSAGE AND ADMINISTRATION

Directions: Adults and children 2 years of
age and older: Brush teeth twice a day, with a
pea size amount for two minutes. Spit out
excess and do not rinse. Wait 30 minutes
before eating or drinking, or as directed by a
dentist or doctor. Instruct children under 6
years of age in good brushing and spitting
habits (to minimize swallowing). Supervise
children as necessary until capable of using
without supervision. Children under 2 years
of age: Consult a dentist or doctor.

Inactive Ingredients: Glycerin, Water,
Hydrated Silica, Xylitol, Nano-Hydroxy apatite,
Cellulose Gum, Spearmint Flavor, Menthol
Crystal, Stevia Rebaudiana Leaf Extract, Citric
Acid, Aloe Barbadensis (Aloe Vera), Illicium
verun (Anise) Extract, Papaya Extract, Prunus
Serotina (Black Cherry) Extract, Glycyrrhiza
Uralensis, (Chinese Licorice) Root Extract,
Mentha Spicata (Spearmint), Mentha Arvensis
(Peppermint), Vitamin K2, Vitamin D3,
Calendula

Dr. Jen SuperPaste Perio Product Package Labeling

++++++++++++++++++++++++++++++++

DR. JEN
SP

Super
Paste

PERIO

10% PREMIUM
NANO-HYDROXYAPATITE,
FLUORIDE & XYLITOL
TOOTHPASTE
___________
Cool Mint
___________

3.4 FL. OZ. | 100 ML
DrJenNatural.com
Dr. Jen
St. Paul, MN 55118

Carton

Tube

res